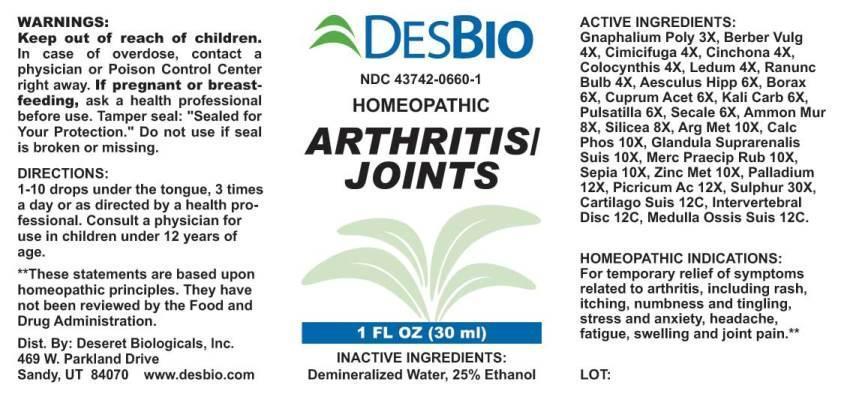 DRUG LABEL: Arthritis Joints
NDC: 43742-0660 | Form: LIQUID
Manufacturer: Deseret Biologicals, Inc.
Category: homeopathic | Type: HUMAN OTC DRUG LABEL
Date: 20170412

ACTIVE INGREDIENTS: PSEUDOGNAPHALIUM OBTUSIFOLIUM 3 [hp_X]/1 mL; BERBERIS VULGARIS ROOT BARK 4 [hp_X]/1 mL; BLACK COHOSH 4 [hp_X]/1 mL; CINCHONA OFFICINALIS BARK 4 [hp_X]/1 mL; CITRULLUS COLOCYNTHIS FRUIT PULP 4 [hp_X]/1 mL; LEDUM PALUSTRE TWIG 4 [hp_X]/1 mL; RANUNCULUS BULBOSUS 4 [hp_X]/1 mL; HORSE CHESTNUT 6 [hp_X]/1 mL; SODIUM BORATE 6 [hp_X]/1 mL; CUPRIC ACETATE 6 [hp_X]/1 mL; POTASSIUM CARBONATE 6 [hp_X]/1 mL; PULSATILLA VULGARIS 6 [hp_X]/1 mL; CLAVICEPS PURPUREA SCLEROTIUM 6 [hp_X]/1 mL; AMMONIUM CHLORIDE 8 [hp_X]/1 mL; SILICON DIOXIDE 8 [hp_X]/1 mL; SILVER 10 [hp_X]/1 mL; TRIBASIC CALCIUM PHOSPHATE 10 [hp_X]/1 mL; SUS SCROFA ADRENAL GLAND 10 [hp_X]/1 mL; MERCURIC OXIDE 10 [hp_X]/1 mL; SEPIA OFFICINALIS JUICE 10 [hp_X]/1 mL; ZINC 10 [hp_X]/1 mL; PALLADIUM 12 [hp_X]/1 mL; PICRIC ACID 12 [hp_X]/1 mL; SULFUR 30 [hp_X]/1 mL; SUS SCROFA CARTILAGE 12 [hp_X]/1 mL; SUS SCROFA INTERVERTEBRAL DISC 12 [hp_X]/1 mL; SUS SCROFA BONE MARROW 12 [hp_X]/1 mL
INACTIVE INGREDIENTS: WATER; ALCOHOL

DRUG FACTS:

ACTIVE INGREDIENTS:

Gnaphalium Polycephalum 3X, Berberis Vulgaris 4X, Cimicifuga Racemosa 4X, Cinchona Officinalis 4X, Colocynthis 4X, Ledum Palustre 4X, Ranunculus Bulbosus 4X, Aesculus Hippocastanum 6X, Borax 6X, Cuprum Aceticum 6X, Kali Carbonicum 6X, Pulsatilla 6X, Secale Cornutum 6X, Ammonium Muriaticum 8X, Silicea 8X, Argentum Metallicum 10X, Calcarea Phosphorica 10X, Glandula Suprarenalis Suis 10X, Mercurius Praecipitatus Ruber 10X, Sepia 10X, Zincum Metallicum 10X, Palladium Metallicum 12X, Picricum Acidum 12X, Sulphur 30X, Cartilago Suis 12C, Intervertebral Disc (Suis) 12C, Medulla Ossis Suis 12C.

HOMEOPATHIC INDICATIONS:

For temporary relief of symptoms related to arthritis, including rash, itching, numbness and tingling, stress and anxiety, headache, fatigue, swelling, and joint pain.**

**These statements are based upon traditional homeopathic practice. They have not been reviewed by the Food and Drug Administration.

WARNINGS:

If pregnant or breast-feeding, ask a health professional before use.

Keep out of reach of children. In case of overdose, get medical help or contact a Poison Control Center right away.

Do not use if tamper evident seal is broken or missing. Store in a cool, dry place.

Keep out of reach of children. In case of overdose, get medical help or contact a Poison Control Center right away.

DIRECTIONS:

1-10 drops under the tongue, 3 times a day or as directed by a health professional. Consult a physician for use in children under 12 years of age.

HOMEOPATHIC INDICATIONS:

For temporary relief of symptoms related to arthritis, including rash, itching, numbness and tingling, stress and anxiety, headache, fatigue, swelling, and joint pain.**

**These statements are based upon traditional homeopathic practice. They have not been reviewed by the Food and Drug Administration.

INACTIVE INGREDIENTS:

Demineralized water, 25% Ethanol.

QUESTIONS:

Dist. By: Deseret Biologicals, Inc.

469 W. Parkland Drive

Sandy, UT 84070 www.desbio.com

PACKAGE LABEL DISPLAY:

DESBIO

NDC 43742-0660-1

HOMEOPATHIC

ARTHRITIS
JOINTS

1 FL OZ (30 ml)